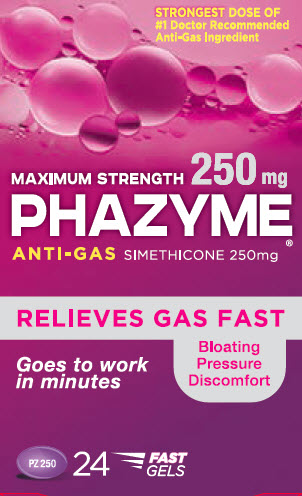 DRUG LABEL: PHAZYME
NDC: 0132-0214 | Form: CAPSULE, GELATIN COATED
Manufacturer: C.B. Fleet Company, Inc.
Category: otc | Type: HUMAN OTC DRUG LABEL
Date: 20170901

ACTIVE INGREDIENTS: DIMETHICONE 250 mg/1 1
INACTIVE INGREDIENTS: D&C RED NO. 33; WATER; GELATIN; FD&C BLUE NO. 1; GLYCERIN; TITANIUM DIOXIDE

Drug Facts

Active Ingredient

(in each softgel)

Simethicone 250mg

Purpose

Anti-gas

Use

relieves bloating, pressure or fullness commonly referred to as gas

Warnings

Stop use and ask a doctor if condition persists

Directions

- swallow one or two softgels after a meal
- do not exceed two softgels per 24 hours except under the advice and supervision of a physician

Other Information

- store at room temperature 59º - 86ºF (15º - 30ºC)

Inactive Ingredients

Red No. 33, FD&C Blue No. 1, Purified Water, Gelatin, Glycerin, Titanium Dioxice

Questions?

Call toll-free 1-855-727-4277